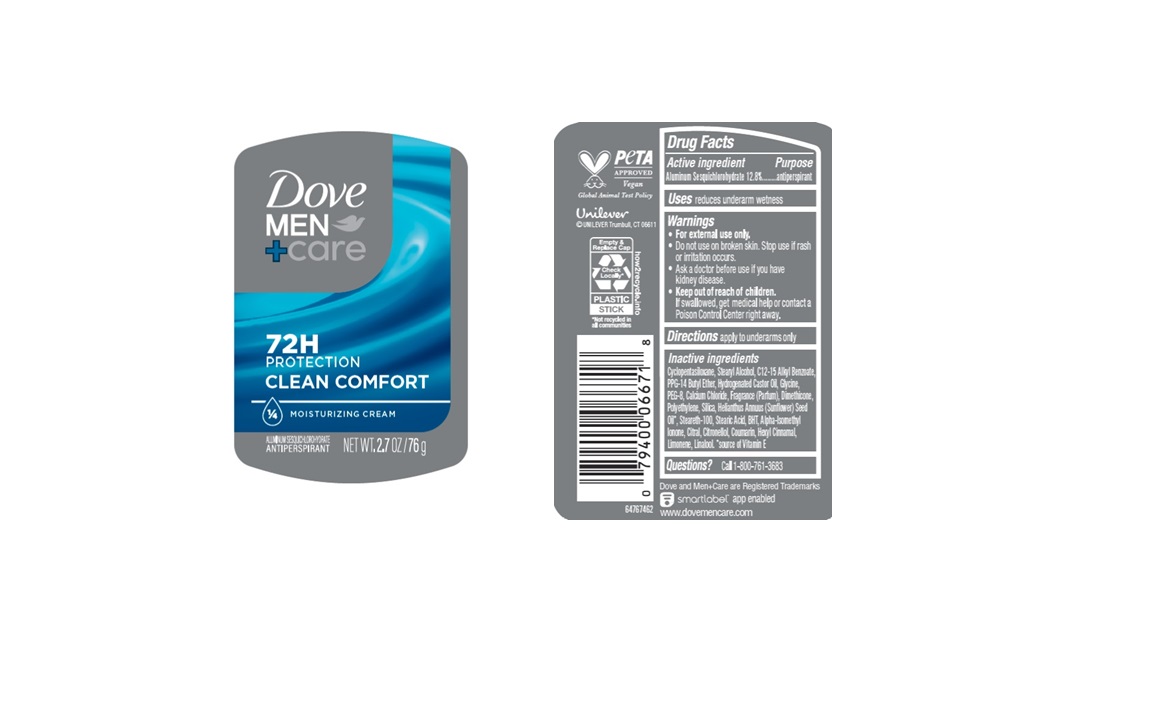 DRUG LABEL: Dove
NDC: 64942-2360 | Form: STICK
Manufacturer: Conopco d/b/a/ Unilever
Category: otc | Type: HUMAN OTC DRUG LABEL
Date: 20250331

ACTIVE INGREDIENTS: ALUMINUM SESQUICHLOROHYDRATE 12.8 g/100 g
INACTIVE INGREDIENTS: POLYETHYLENE; HELIANTHUS ANNUUS (SUNFLOWER) SEED OIL; STEARETH-100; PPG-14 BUTYL ETHER; STEARIC ACID; HYDROGENATED CASTOR OIL; ALPHA-ISOMETHYL IONONE; LINALOOL, (+/-)-; BHT; CITRAL; HEXYL CINNAMAL; SILICA; LIMONENE, (+)-; CALCIUM CHLORIDE; CITRONELLOL; CYCLOPENTASILOXANE; STEARYL ALCOHOL; GLYCINE; C12-15 ALKYL BENZOATE; PEG-8; DIMETHICONE; COUMARIN

Dove Men + Care Clean Comfort 72H Antiperspirant

DESCRIPTION

Dove Men + Care Clean Comfort 72H Antiperspirant

ACTIVE INGREDIENT

Aluminum Sesquichlorohydrate (12.8%)

PURPOSE

antiperspirant

INDICATIONS AND USAGE

reduces underarm wetness

WARNINGS

For external use only.

Do not use on broken skin. Stop use if rash or irritation occurs.

Ask a doctor before use if you have kidney disease.

Keep out of reach of children. If swallowed, get medical help or contact a Poison Control Center right away.

DOSAGE AND ADMINISTRATION

apply to underarms only

INACTIVE INGREDIENT

Cyclopentasiloxane, Stearyl Alcohol, C12-15 Alkyl Benzoate, PPG-14 Butyl Ether, Hydrogenated Castor Oil, Glycine, PEG-8, Calcium Chloride, Fragrance (Parfum), Dimethicone, Polyethylene, Silica, Helianthus Annuus (Sunflower) Seed Oil, Steareth-100, Stearic Acid, BHT, Alpha-Isomethyl Ionone, Citral, Citronellol, Coumarin, Hexyl Cinnamal, Limonene, Linalool.

QUESTIONS

Call 1-800-761-3683